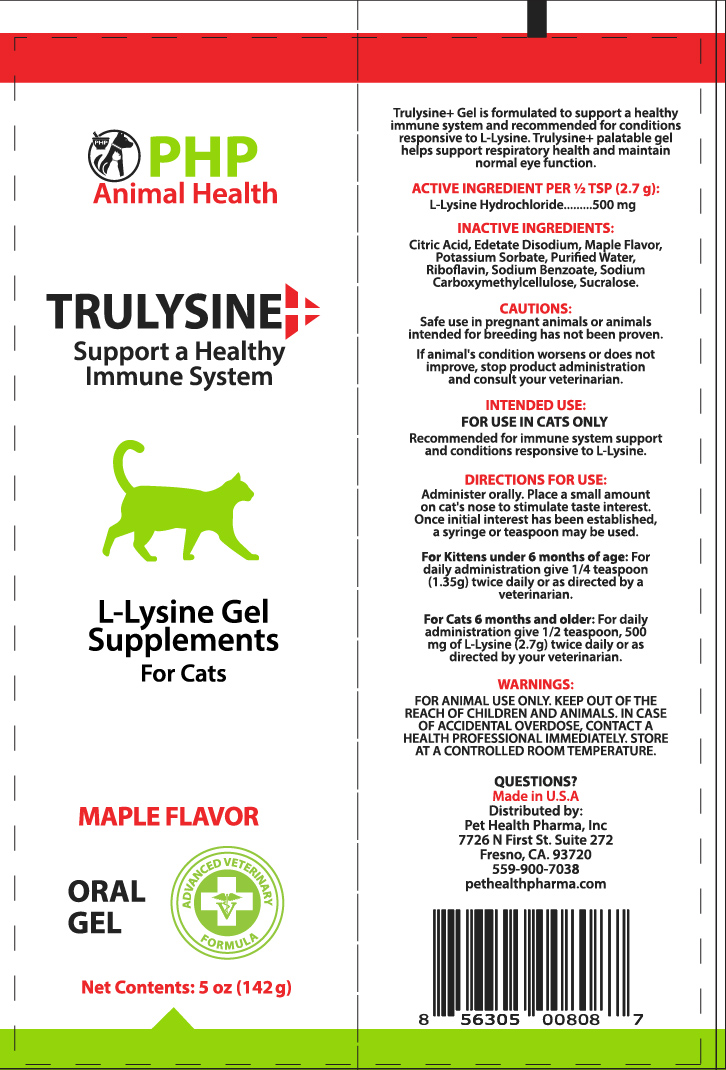 DRUG LABEL: TRULYSINE
NDC: 86176-306 | Form: GEL
Manufacturer: Pet Health Pharma, LLC
Category: animal | Type: OTC ANIMAL DRUG LABEL
Date: 20250826

ACTIVE INGREDIENTS: LYSINE HYDROCHLORIDE 500 mg/1 g
INACTIVE INGREDIENTS: CITRIC ACID MONOHYDRATE; EDETATE DISODIUM; POTASSIUM SORBATE; WATER; RIBOFLAVIN; SODIUM BENZOATE; CARBOXYMETHYLCELLULOSE SODIUM, UNSPECIFIED; SUCRALOSE

Trulysine for cats

Product Facts

L-Lysine Hydrochloride...............500 mg per 2.7g

INACTIVE INGREDIENTS:

Citric Acid, Edetate Disodium, Maple Flavor, Potassium Sorbate, Purified Water, Riboflavin, Sodium Benzoate, Sodium Carboxymethylcellulose, Sucralose.

CAUTIONS:

Safe use in pregnant animals or animals intended for breeding has not been proven.

If animal's condition worsens or does not improve, stop product administration and consult your veterinarian.

INTENDED USE:

FOR USE IN CATS ONLY

Recommended for immune system support and conditions responsive to L-Lysine.

DIRECTIONS FOR USE:

Administer orally. Place a small amount on cat's nose to stimulate taste interest. Once initial interest has been established, a syringe or teaspoon may be used.

For Kitttens under 6 months of age: For daily administrationgive 1/4 teaspoon, (1.35g) twice daily or as directed by your veterinarian.

For cats 6 months and older: For daily administration give 1/2 teaspoon, 500mg of L-Lysine (2.7g) twice daily or as directed by your veterinarian.

WARNINGS:

FOR ANIMAL USE ONLY. KEEP OUT OF THE REACH OF CHILDREN AND ANIMALS. IN CASE OF ACCIDENTAL OVERDOSE, CONTACT A HEALTH PROFESSIONAL IMMEDIATELY. STORE AT A CONTROLLED ROOM TEMPERATURE.

QUESTIONS:

Made in U.S.A

Distributed by:

Pet Health Pharma, Inc.

7726 N First St. Suite 272

Fresno, CA 93720

559-900-7038

pethealthpharma.com